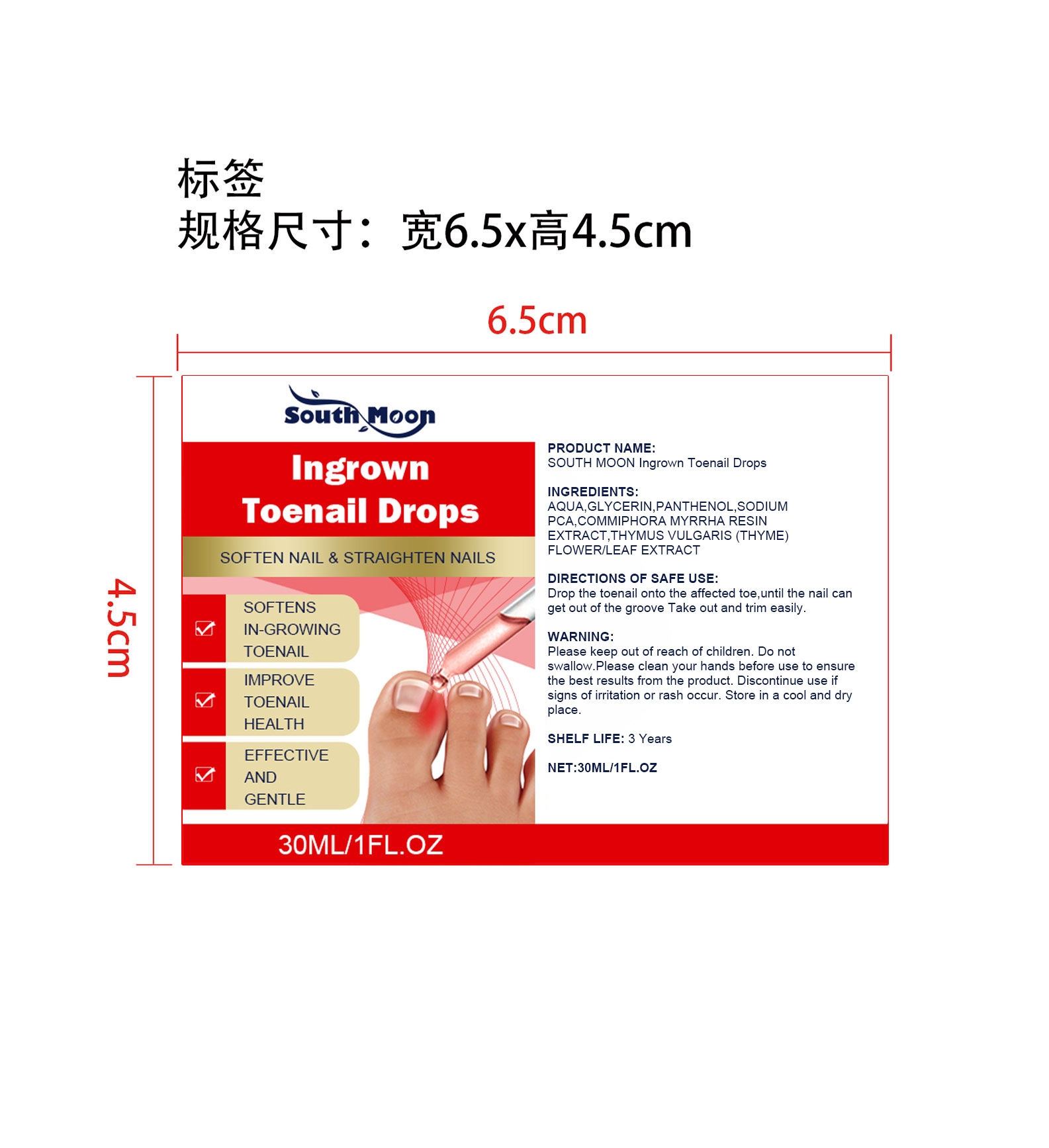 DRUG LABEL: SOUTH MOON Ingrown Toenail Drops
NDC: 84983-014 | Form: LIQUID
Manufacturer: Shantou South Moon Biotechnology Co., Ltd.
Category: otc | Type: HUMAN OTC DRUG LABEL
Date: 20251127

ACTIVE INGREDIENTS: THYMUS VULGARIS (THYME) FLOWER/LEAF OIL 0.006 mg/30 mg; COMMIPHORA MYRRHA RESIN 0.006 mg/30 mg
INACTIVE INGREDIENTS: SODIUM PCA 0.3 mg/30 mg; PANTHENOL 0.45 mg/30 mg; GLYCERIN 1.2 mg/30 mg; AQUA 28.038 mg/30 mg

ACTIVE INGREDIENT

COMMIPHORA MYRRHA RESIN、THYMUS VULGARIS (THYME) FLOWER/LEAF OIL

WHEN USING

Drop the toenail onto the affected toe,until the nail can get out of the groove Take out and trim easily.

PURPOSE

SOFTENS IN-GROWING TOENAIL
IMPROVE TOENAIL HEALTH
EFFECTIVE AND GENTLE

WARNINGS

Please keep out of reach of children. Do not swallow.Please clean your hands before use to ensure the best results from the product. Discontinue use if signs of irritation or rash occur. Store in a cool and dry place.

DO NOT USE

Discontinue use if signs of irritation or rash occur.

STOP USE

Discontinue use if signs of irritation or rash occur.

KEEP OUT OF REACH OF CHILDREN

Please keep out of reach of children. Do not swallow.

STORAGE AND HANDLING

Store in a cool and dry place.

INACTIVE INGREDIENT

AQUA、GLYCERIN、PANTHENOL、SODIUM PCA

DOSAGE AND ADMINISTRATION

Drop the toenail onto the affected toe,until the nail can get out of the groove Take out and trim easily.

INDICATIONS AND USAGE

Drop the toenail onto the affected toe,until the nail can get out of the groove Take out and trim easily.